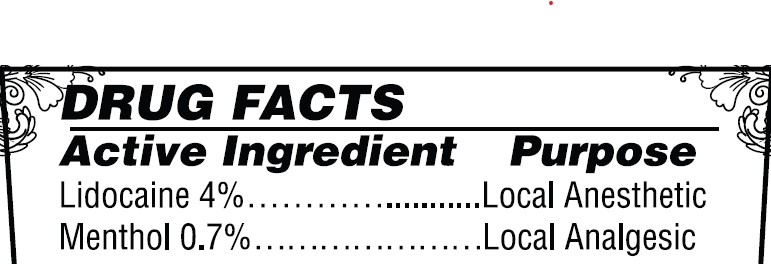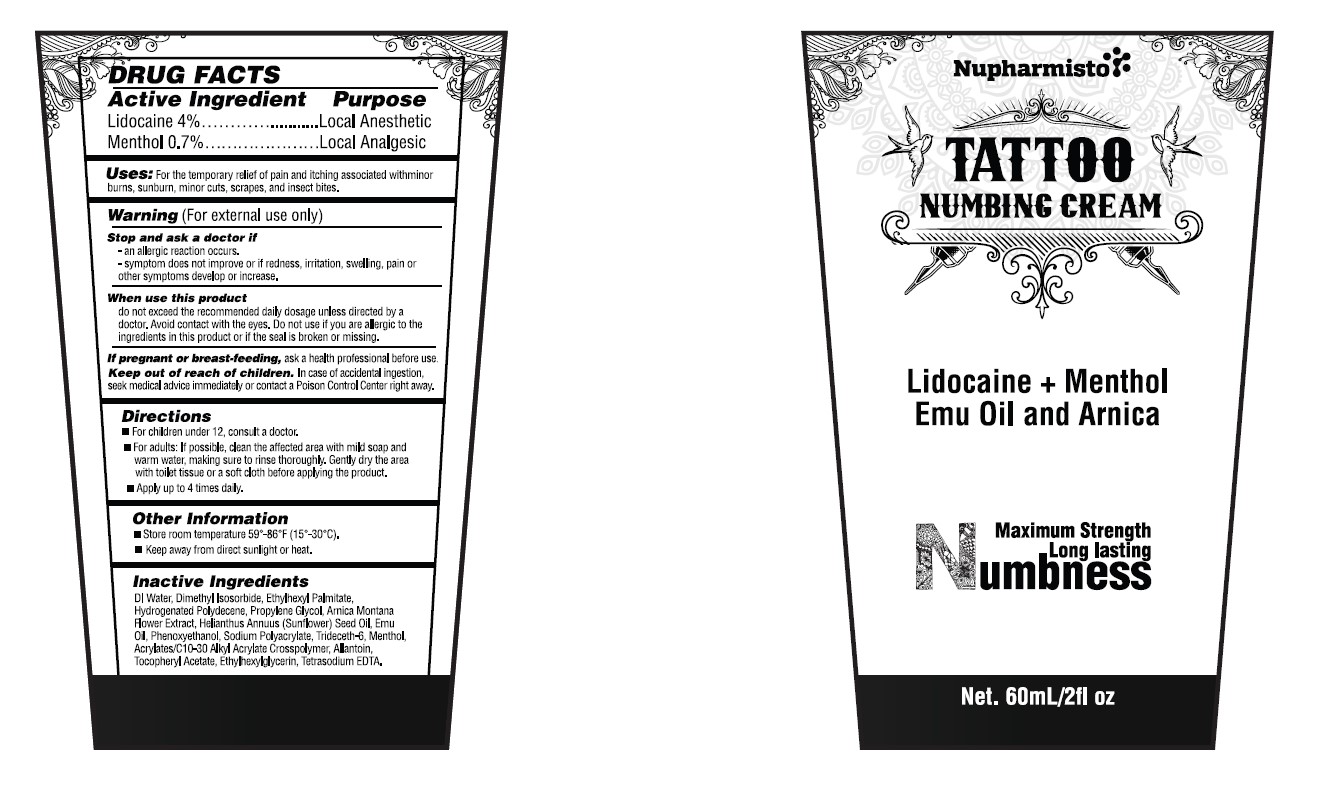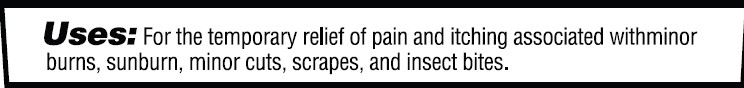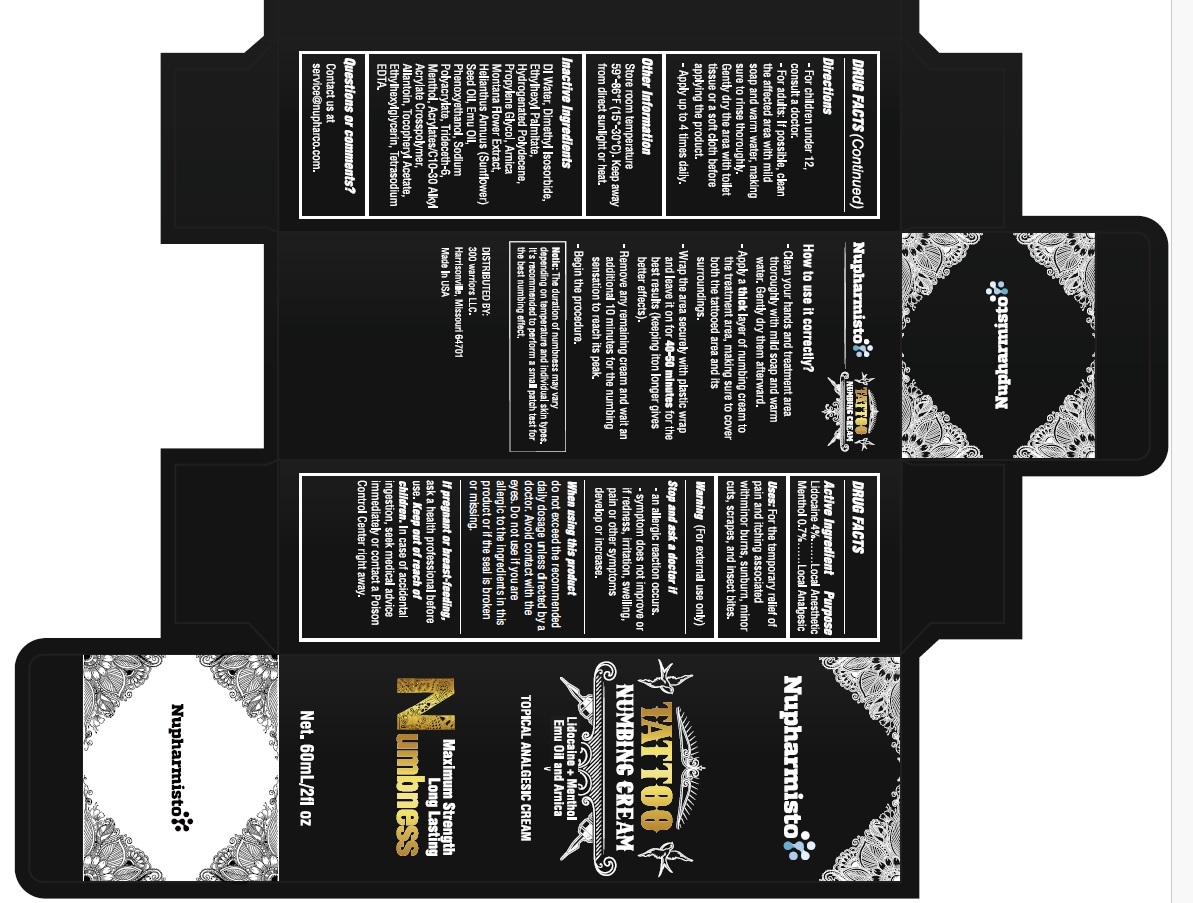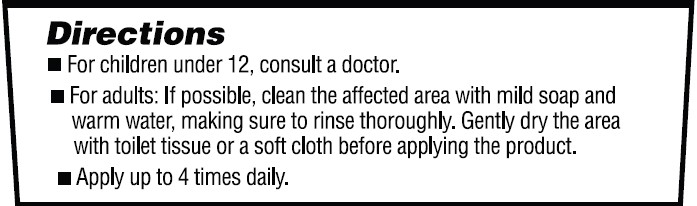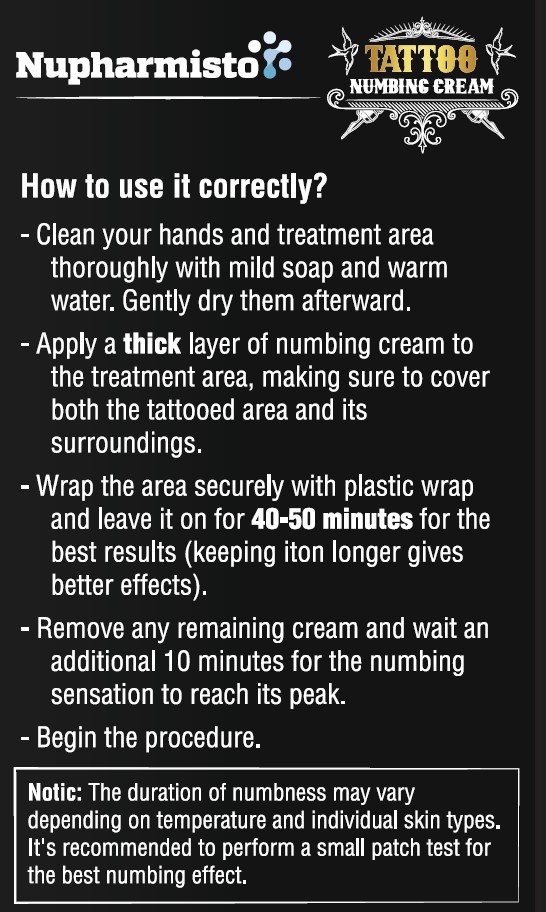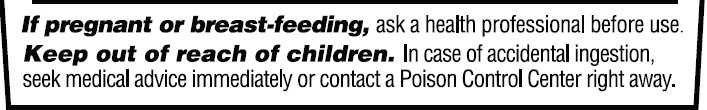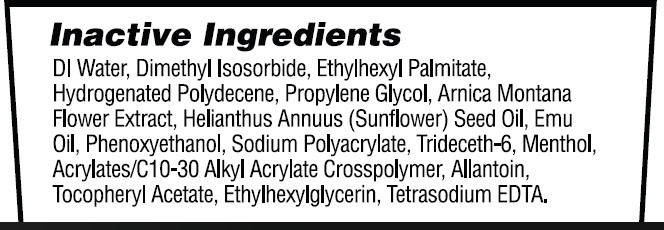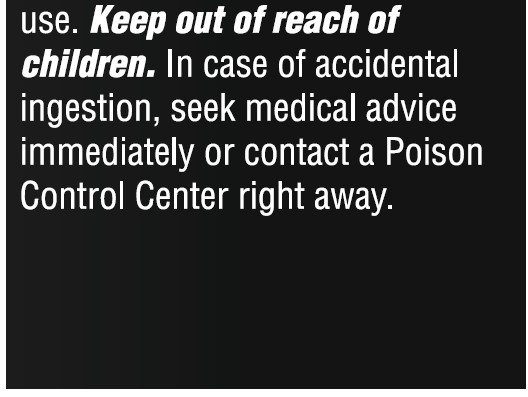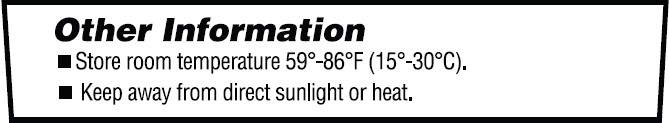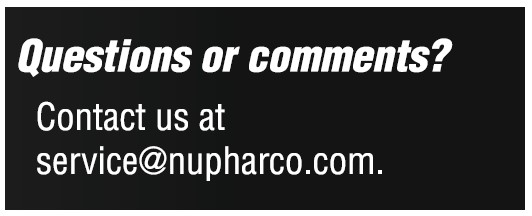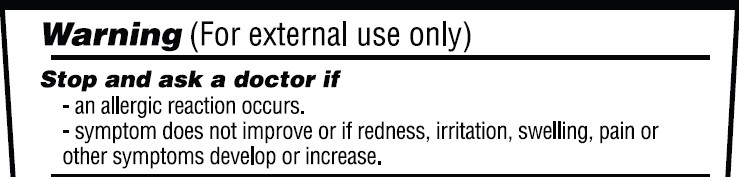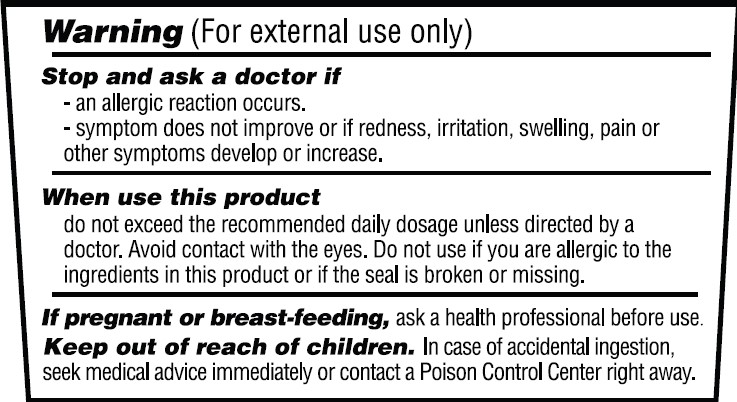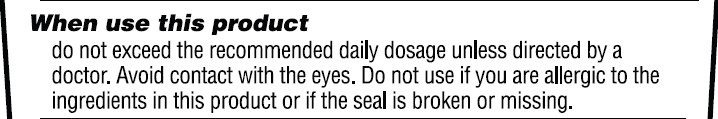 DRUG LABEL: Nupharmisto Tattoo Numbing Cream 60ml
NDC: 71331-119 | Form: CREAM
Manufacturer: Orange Lab, Inc
Category: otc | Type: HUMAN OTC DRUG LABEL
Date: 20240901

ACTIVE INGREDIENTS: LIDOCAINE 4 g/100 g; MENTHOL 0.7 g/100 g
INACTIVE INGREDIENTS: ARNICA MONTANA FLOWER; ALLANTOIN; ETHYLHEXYLGLYCERIN; WATER; PROPYLENE GLYCOL; EMU OIL; TRIDECETH-6; ACRYLATES/C10-30 ALKYL ACRYLATE CROSSPOLYMER (60000 MPA.S); HYDROGENATED POLYDECENE (1500 CST); SUNFLOWER OIL UNSAPONIFIABLES; ETHYLHEXYL PALMITATE; PHENOXYETHANOL; SODIUM POLYACRYLATE (8000 MW); .ALPHA.-TOCOPHEROL ACETATE; DIMETHYL ISOSORBIDE; EDETATE SODIUM

Nupharmisto Tattoo Numbing Cream 60ml